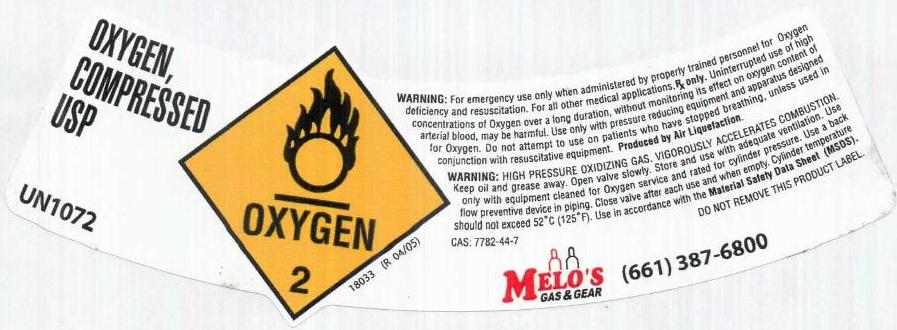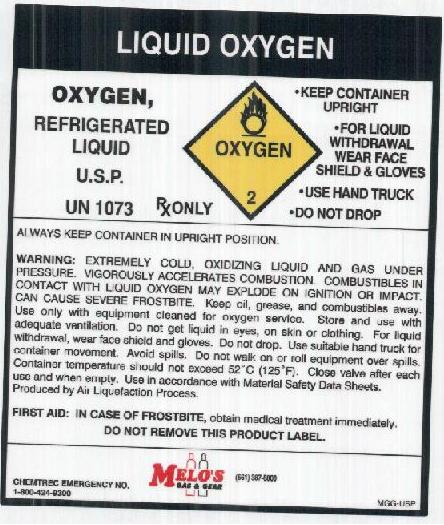 DRUG LABEL: Oxygen
NDC: 24533-001 | Form: GAS
Manufacturer: Melo's Gas and Gear, Inc.
Category: prescription | Type: HUMAN PRESCRIPTION DRUG LABEL
Date: 20120207

ACTIVE INGREDIENTS: Oxygen 990 mL/1 L

Oxygen Label

PACKAGE LABEL

LIQUID OXYGEN
OXYGEN, REFRIGERATED LIQUID U.S.P. UN 1073 RX ONLY OXYGEN 2
KEEP CONTAINER UPRIGHT
FOR LIQUID WITHDRAWAL WEAR FACE SHIELD and GLOVES
USE HAND TRUCK
DO NOT DROP
ALWAYS KEEP CONTAINER IN UPRIGHT POSITION.
WARNING: EXTREMELY COLD, OXIDIZING LIQUID AND GAS UNDER PRESSURE. VIGOROUSLY ACCELERATES COMBUSTION. COMBUSTIBLES IN CONTACT WITH LIQUID OXYGEN MAY EXPLODE ON IGNITION OR IMPACT. CAN CAUSE SEVERE FROSTBITE. Keep oil, grease, and combustibles away. Use only with equipment cleaned for oxygen service. Store and use with adequate ventilation. Do not get liquid in eyes, on skin, or clothing. For liquid withdrawal, wear face shield and gloves. Do not drop. Use suitable hand truck for container movement. Avoid spills. Do not walk on or roll equipment over spills. Cylinder temperature should not exceed 52C (125F). Close valve after each use and when empty. Use in accordance with the Material Safety Data Sheet. Produced by Air Liquefaction Process.
FIRST AID: IN CASE OF FROSTBITE, obtain medical treatment immediately.
DO NOT REMOVE THIS PRODUCT LABEL.
CHEMTREC EMERGENCY NO. 1-800-424-9300
MELO’S GAS AND GEAR (661) 387-6800
MGG-USP

PACKAGE LABEL

OXYGEN, COMPRESSED USP UN1072
OXYGEN 2 18033 (R 04/05)
WARNING: For emergency use only when administered by properly trained personnel for Oxygen deficiency and resuscitation. For all other medical applications, Rx only. Uninterrupted use of high concentrations of oxygen over a long duration, without monitoring its effect on Oxygen content of arterial blood, may be harmful. Use only with pressure reducing equipment and apparatus designed for use with Oxygen. Do not attempt to use on patients who have stopped breathing, unless used in conjunction with resuscitative equipment. PRODUCED BY AIR LIQUEFACTION.
WARNING: HIGH PRESSURE OXIDIZING GAS. VIGOROUSLY ACCELERATES COMBUSTION. Keep oil and grease away. Open valve slowly. Store and use with adequate ventilation. Use only with equipment cleaned for Oxygen service and rated for cylinder pressure. Use a back flow preventive device in piping. Close valve after each use and when empty. Cylinder temperature should not exceed 52C (125F). Use in accordance with the Material Safety Data Sheet (MSDS).
CAS: 7782-44-7 DO NOT REMOVE THIS PRODUCT LABEL.
MELO’S GAS AND GEAR (661) 387-6800